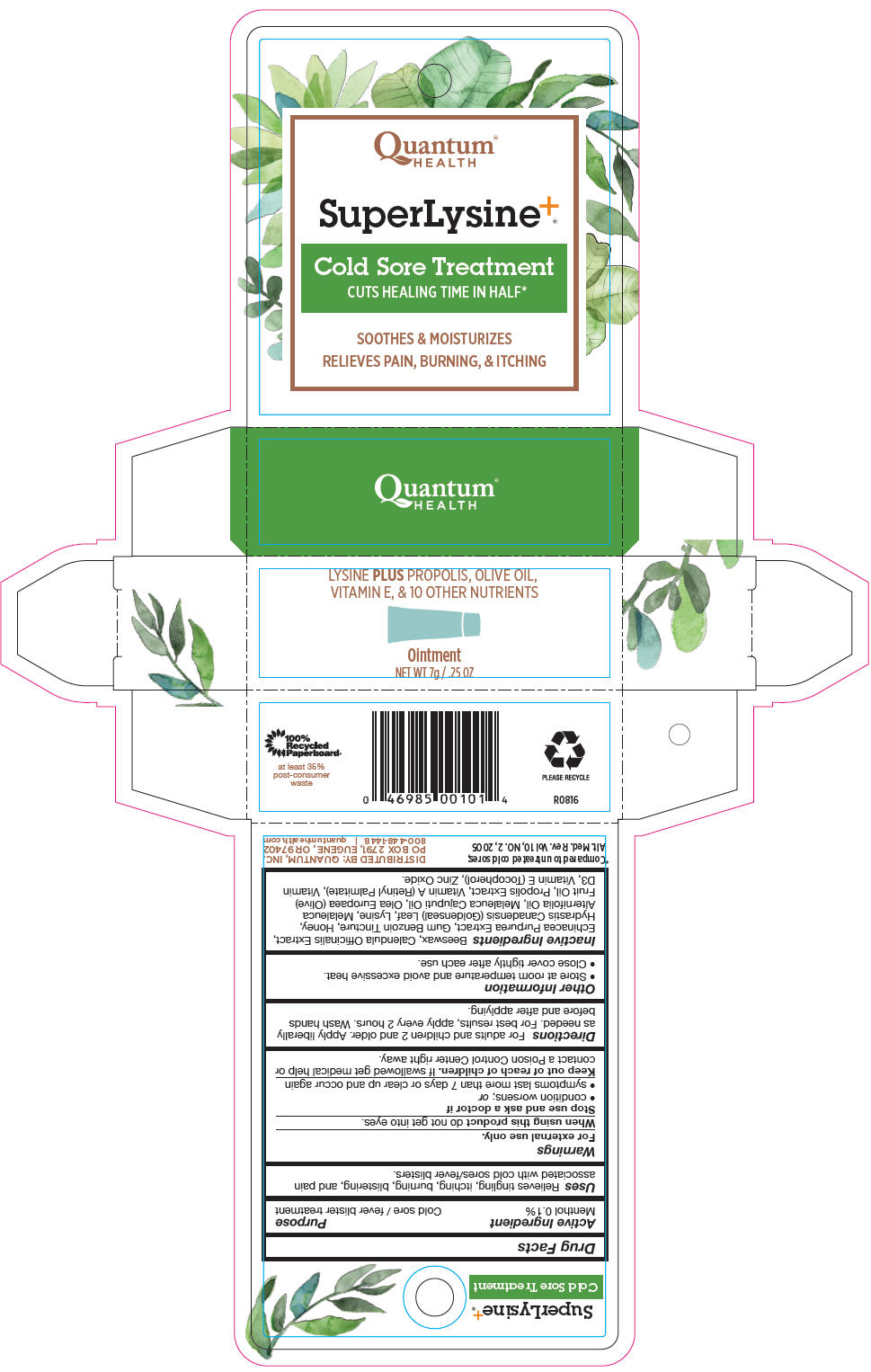 DRUG LABEL: Super Lysine plus
NDC: 70084-420 | Form: OINTMENT
Manufacturer: Quantum, Inc.
Category: otc | Type: HUMAN OTC DRUG LABEL
Date: 20230207

ACTIVE INGREDIENTS: Menthol, Unspecified Form 1 mg/1 g
INACTIVE INGREDIENTS: Calendula Officinalis Flower; Echinacea Purpurea; BENZOIN RESIN; HONEY; GOLDENSEAL; LYSINE HYDROCHLORIDE; TEA TREE OIL; MELALEUCA CAJUPUTI LEAF OIL; OLIVE OIL; PROPOLIS WAX; VITAMIN A PALMITATE; CHOLECALCIFEROL; .ALPHA.-TOCOPHEROL; ZINC OXIDE; Yellow Wax

Super Lysine^+®

Drug Facts

Active Ingredient

Menthol 0.1%

Purpose

Cold sore / fever blister treatment

Uses

Relieves tingling, itching, burning, blistering, and pain associated with cold sores/fever blisters.

Warnings

For external use only.

When using this product do not get into eyes.

Stop use and ask a doctor if

- condition worsens; or
- symptoms last more than 7 days or clear up and occur again

Keep out of reach of children. If swallowed get medical help or contact a Poison Control Center right away.

Directions

For adults and children 2 and older. Apply liberally as needed. For best results, apply every 2 hours. Wash hands before and after applying.

Other Information

- Store at room temperature and avoid excessive heat.
- Close cover tightly after each use.

Inactive Ingredients

Beeswax, Calendula Officinalis Extract, Echinacea Purpurea Extract, Gum Benzoin Tincture, Honey, Hydrastis Canadensis (Goldenseal) Leaf, Lysine, Melaleuca Alternifolia Oil, Melaleuca Cajuputi Oil, Olea Europaea (Olive) Fruit Oil, Propolis Extract, Vitamin A (Retinyl Palmitate), Vitamin D3, Vitamin E (Tocopherol), Zinc Oxide.

DISTRIBUTED BY: QUANTUM, INC.
PO BOX 2791, EUGENE, OR 97402

PRINCIPAL DISPLAY PANEL - 7 g Tube Carton

Quantum®
HEALTH

SuperLysine^+®

Cold Sore Treatment
CUTS HEALING TIME IN HALF*

SOOTHES & MOISTURIZES
RELIEVES PAIN, BURNING, & ITCHING

LYSINE PLUS PROPOLIS, OLIVE OIL,
VITAMIN E, & 10 OTHER NUTRIENTS

Ointment

NET WT 7g / .25 OZ